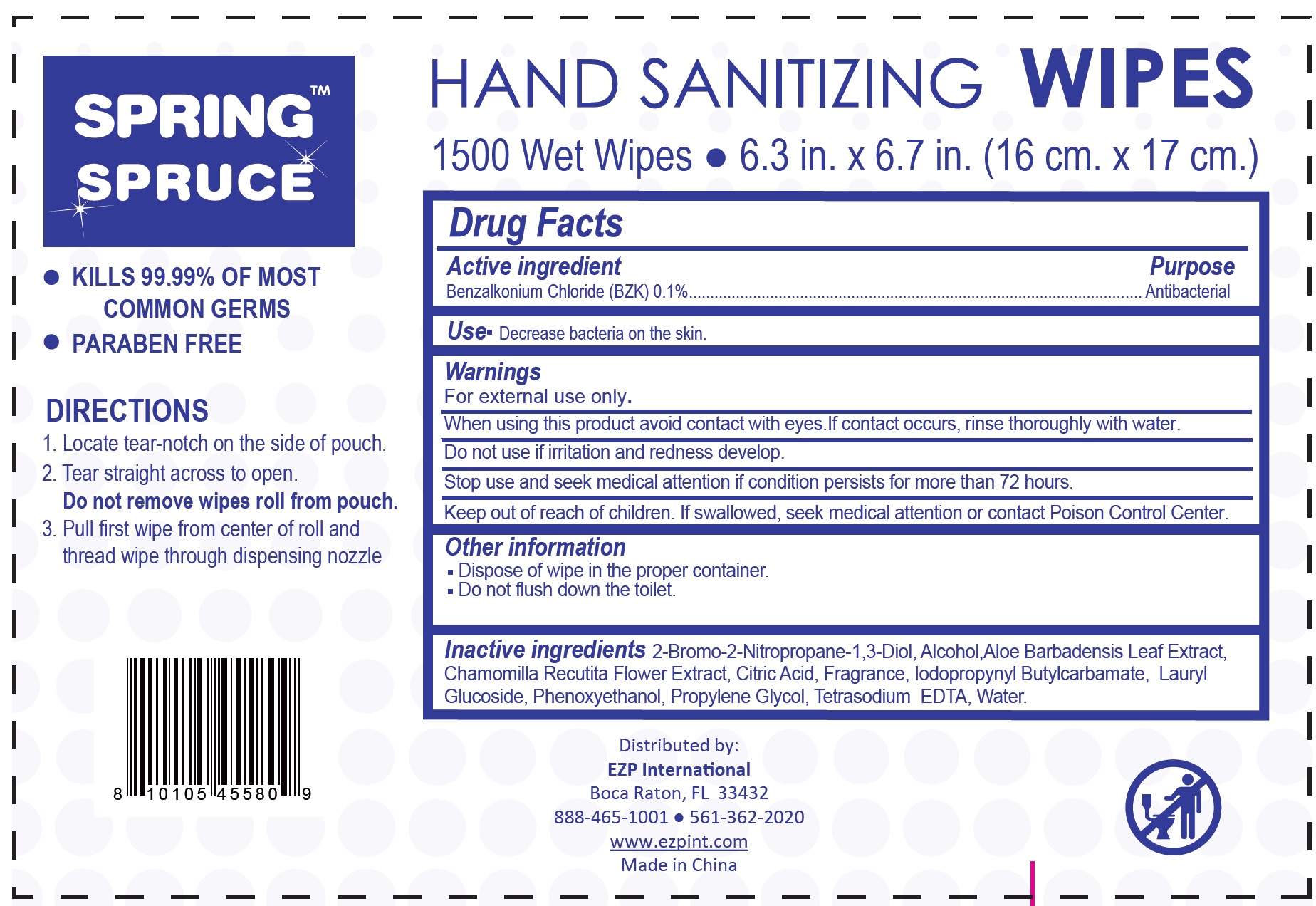 DRUG LABEL: Hand Sanitizing Wipes
NDC: 69446-220 | Form: CLOTH
Manufacturer: Ez Products Of South Florida, LLC
Category: otc | Type: HUMAN OTC DRUG LABEL
Date: 20231023

ACTIVE INGREDIENTS: BENZALKONIUM CHLORIDE 1 mg/1 g
INACTIVE INGREDIENTS: BRONOPOL; ALCOHOL; ALOE VERA LEAF; CHAMOMILE; CITRIC ACID MONOHYDRATE; IODOPROPYNYL BUTYLCARBAMATE; LAURYL GLUCOSIDE; PHENOXYETHANOL; PROPYLENE GLYCOL; EDETATE SODIUM; WATER

Hand Sanitizing Wipes

Active ingredient

Benzalkonium Chloride (BZK) 0.1%

Purpose

Antibacterial

Use

- Decrease bacteria on the skin.

Warnings

For external use only.

When using this product

avoid contact with eyes.If contact occurs, rinse thoroughly with water.

Do not use

if irritation and redness develop.

Stop use and seek medical attention

if condition persists for more than 72 hours.

Keep out of reach of children.

If swallowed, seek medical attention or contact Poison Control Center.

DIRECTIONS

1. Locate tear-notch on the side of pouch. 2. Tear straight across to open. 3. Pull first wipe from center of roll and thread wipe through dispensing nozzle
Do not remove wipes roll from pouch.

Other information

- Dispose of wipe in the proper container.
- Do not flush down the toilet.

Inactive ingredients

2-Bromo-2-Nitropropane-1,3-Diol, Alcohol,Aloe Barbadensis Leaf Extract, Chamomilla Recutita Flower Extract, Citric Acid, Fragrance, Iodopropynyl Butylcarbamate, Lauryl Glucoside, Phenoxyethanol, Propylene Glycol, Tetrasodium EDTA, Water.